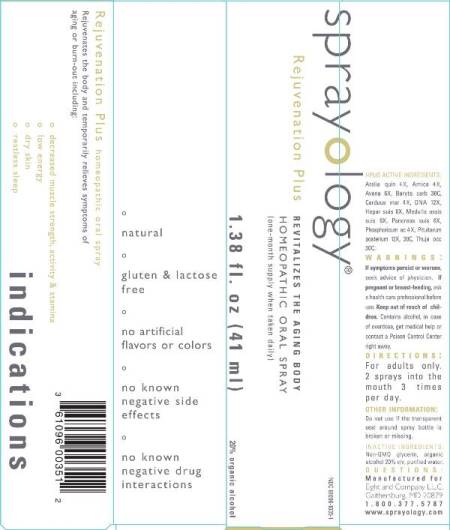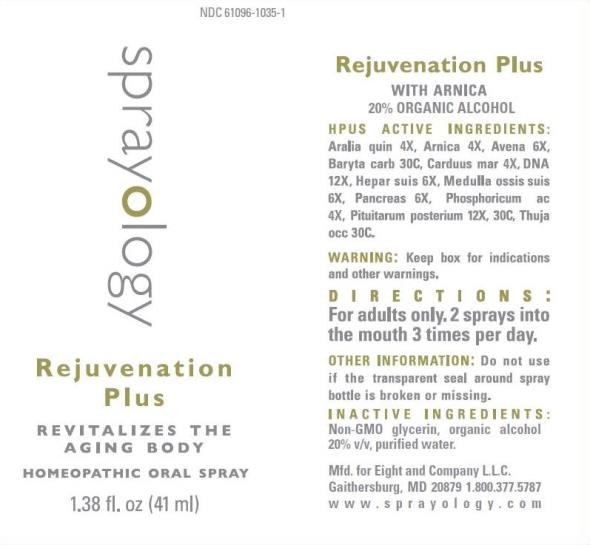 DRUG LABEL: Rejuvenation Plus
NDC: 61096-1035 | Form: LIQUID
Manufacturer: Eight and Company L.L.C
Category: homeopathic | Type: HUMAN OTC DRUG LABEL
Date: 20251218

ACTIVE INGREDIENTS: AMERICAN GINSENG 4 [hp_X]/41 mL; ARNICA MONTANA WHOLE 4 [hp_X]/41 mL; AVENA SATIVA FLOWERING TOP 6 [hp_X]/41 mL; BARIUM CARBONATE 30 [hp_C]/41 mL; MILK THISTLE 4 [hp_X]/41 mL; HERRING SPERM DNA 12 [hp_X]/41 mL; PORK LIVER 6 [hp_X]/41 mL; SUS SCROFA BONE MARROW 6 [hp_X]/41 mL; SUS SCROFA PANCREAS 6 [hp_X]/41 mL; PHOSPHORIC ACID 4 [hp_X]/41 mL; SUS SCROFA PITUITARY GLAND 12 [hp_X]/41 mL; THUJA OCCIDENTALIS LEAFY TWIG 30 [hp_C]/41 mL
INACTIVE INGREDIENTS: GLYCERIN; ALCOHOL; WATER

Rejuvenation Plus

ACTIVE INGREDIENTS:

Aralia quin 4X, Arnica 4X, Avena 6X, Baryta carb 30C, Carduus mar 4X, DNA 12X, Hepar suis 6X, Medulla ossis suis 6X, Pancreas suis 6X, Phosphoricum ac 4X, Pituitarum posterium 12X, 30C, Thuja occidentalis 30C.

PURPOSE:

Rejuvenates the body and temporarily relieves symptoms of aging or burn-out including:

- decreased muscle strength, activity & stamina
- low energy
- dry skin
- restless sleep

WARNINGS:

If symptoms persist or worsen, seek advice of physician. If pregnant or breast-feeding, ask a health care professional before use. Keep out of reach of children. Contains alcohol, in case of overdose, get medical help or contact a Poison Control Center right away.

Keep out of reach of children. Contains alcohol, in case of overdose, get medical help or contact a Poison Control Center right away.

DIRECTIONS:

For adults only. 2 sprays into the mouth 3 times per day.

OTHER INFORMATION:

Do not use if the transparent seal around spray bottle is broken or missing.

INDICATIONS:

Rejuvenates the body and temporarily relieves symptoms of aging or burn-out including:

° low energy

° dry skin

° restless sleep

° decreased muscle strength, activity & stamina

° natural

° gluten & lactose free

° no artificial flavors or colors

° no known negative side effects

° no known negative drug interactions

INACTIVE INGREDIENTS:

Non-GMO glycerin v/v, organic alcohol 20% v/v and purified water.

QUESTIONS:

Mfd. for Eight and Company L.L.C.

Gaithersburg, MD 20879 1.800.377.5787

www.sprayology.com

PACKAGE LABEL DISPLAY:

NDC 61096-1035-1

sprayology

REJUVENATION PLUS

REVITALIZES THE AGING BODY

HOMEOPATHIC ORAL SPRAY

1.38 fl.oz (41 ml)